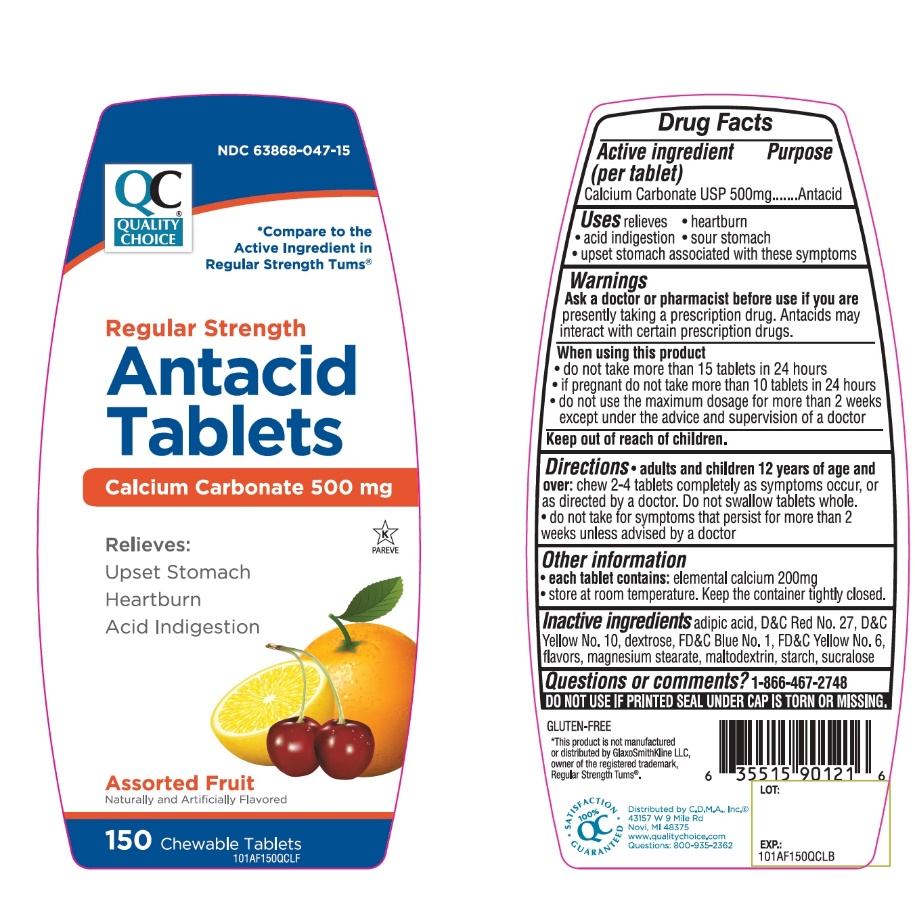 DRUG LABEL: Quality Choice Chewable Antacid

NDC: 63868-047 | Form: TABLET, CHEWABLE
Manufacturer: Chain Drug Marketing Association
Category: otc | Type: HUMAN OTC DRUG LABEL
Date: 20251203

ACTIVE INGREDIENTS: CALCIUM CARBONATE 500 mg/1 1
INACTIVE INGREDIENTS: ADIPIC ACID; D&C RED NO. 27; D&C YELLOW NO. 10; DEXTROSE, UNSPECIFIED FORM; FD&C BLUE NO. 1; FD&C YELLOW NO. 6; MAGNESIUM STEARATE; MALTODEXTRIN; STARCH, CORN; SUCRALOSE

Drug Facts

Active ingredient

Calcium carbonates USP 500mg

Purpose

Antacid

Uses

relieves:

• heartburn

• sour stomach

• acid indigestion

• upset stomach associated with these symptoms

Warnings

Ask a doctor or pharmacist before use if you aretaking a prescription drug. Antacids may interact with certain prescription drugs.

When using this product

• do not take more than 15 tablets in 24 hours

• do not use the maximum dosage for more than 2 weeks.

Directions

• Chew 2-4 tablets as symptoms occur, or as directed by a doctor.

Other Information

• Store below 30°C (86°F).

• Keep the container tightly closed

• For calcium and magnesium content see Supplement Facts.

Inactive ingredients

adipic acid, D&C Red No. 27, D&C Yellow No. 10, dextrose, FD&C Blue No. 1, FD&C Yellow No. 6, flavors, magnesium stearate, maltodextrin, starch, sucralose.

Safety sealed: Do not use if printed seal under cap is torn or missing

Package/Label Principal Display Panel

Compare to Tums Regular Strength active ingredient*

NDC 63868-047-15

Quality Choice

Regular Strength

Antacid Tablets

Antacid Calcium Supplement

Calcium Carbonate 500mg

Relieves:

Upset Stomach

Heartburn

Acid Indigestion

Assorted Fruit

150 Chewable Tablets

Quality Choice Regular Strength Antacid Tablets